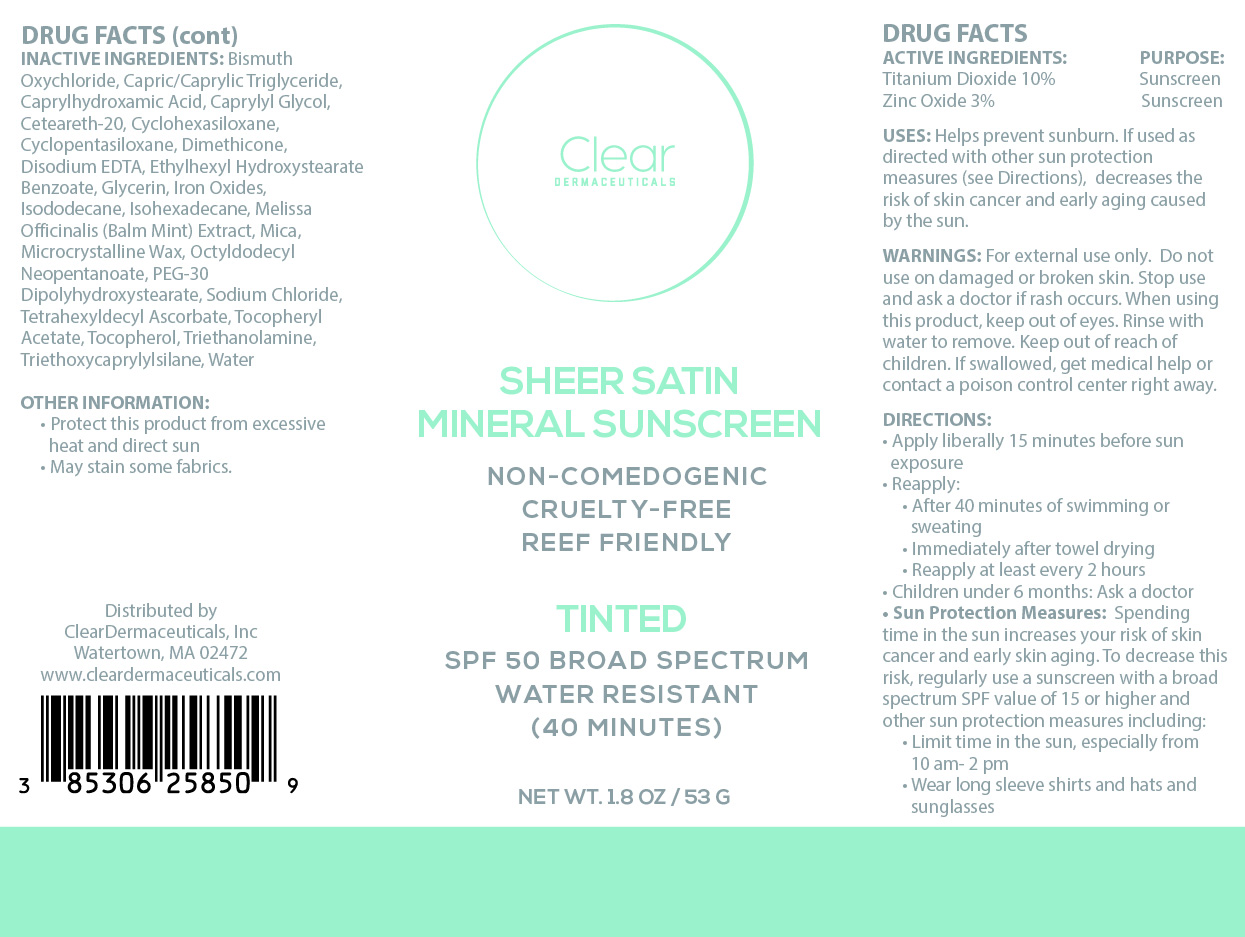 DRUG LABEL: Sheer Satin Mineral Sunscreen Tinted
NDC: 85306-258 | Form: CREAM
Manufacturer: INTEGRATIVE AESTHETICS BOSTON, LLC
Category: otc | Type: HUMAN OTC DRUG LABEL
Date: 20251209

ACTIVE INGREDIENTS: TITANIUM DIOXIDE 100 mg/1 g; ZINC OXIDE 30 mg/1 g
INACTIVE INGREDIENTS: CI 77491; TOCOPHEROL; MELISSA OFFICINALIS LEAF; PEG-30 DIPOLYHYDROXYSTEARATE; MICROCRYSTALLINE WAX; SODIUM CHLORIDE; CAPRYLIC/CAPRIC TRIGLYCERIDE; CAPRYLYL GLYCOL; CYCLOPENTASILOXANE; EDETATE DISODIUM ANHYDROUS; CYCLOHEXASILOXANE; CI 77492; ISOHEXADECANE; ALPHA-TOCOPHEROL ACETATE; OCTYLDODECYL NEOPENTANOATE; CETEARETH-20; CI 77499; MICA; TETRAHEXYLDECYL ASCORBATE; TRIETHOXYCAPRYLYLSILANE; WATER; CAPRYLHYDROXAMIC ACID; BISMUTH OXYCHLORIDE; DIMETHICONE; ETHYLHEXYL HYDROXYSTEARATE BENZOATE; TRIETHANOLAMINE; GLYCERIN; ISODODECANE

Active Ingredients:

Titanium Dioxide 10% Zinc Oxide 3%

Purpose:

Sunscreen

Uses:

Helps prevents sunburn. If used as directed with other sun protection measures (see Directions), decreases the risk of skin cancer and early skin aging caused by the sun.

Warnings:

For external use only. Do not use on damaged or broken skin. Stop use and ask a doctor if rash occurs. When using this product, keep out of eyes. Rinse with water to remove. Keep out of the reach of children. If swallowed, get medical help or contact a poison control center right away.

Warnings:

Keep out of reach of children

Directions:

• Apply liberally 15 minutes before sun exposure. • Reapply: • After 80 minutes of swimming or sweating • Immediately after towel drying • At least every 2 hours • Children under 6 months: Ask a doctor • Sun Protection Measures: Spending time in the sun increases your risk of skin cancer and early skin aging. To decrease this risk, regularly use a sunscreen with a Broad Spectrum SPF value of 15 or higher and other sun protection measures including: •Limit time in the sun, especially from 10 am-2 pm •Wear long-sleeved shirts, pants, hats, and sunglasses

Inactive Ingredients:

Bismuth Oxychloride, Capric/Caprylic Triglyceride, Caprylhydroxamic Acid, Caprylyl Glycol, Ceteareth-20, Cyclohexasiloxane, Cyclopentasiloxane, Dimethicone, Disodium EDTA, Ethylhexyl Hydroxystearate Benzoate, Glycerin, Iron Oxides, Isododecane, Isohexadecane, Melissa Officinalis (Balm Mint) Extract, Mica, Microcrystalline Wax, Octyldodecyl Neopentanoate, PEG-30 Dipolyhydroxystearate, Sodium Chloride, Tetrahexyldecyl Ascorbate, Tocopheryl Acetate, Tocopherol, Triethanolamine, Triethoxycaprylylsilane, Water

Other Information:

Protect this product from excessive heat and direct sun. May stain some fabrics.